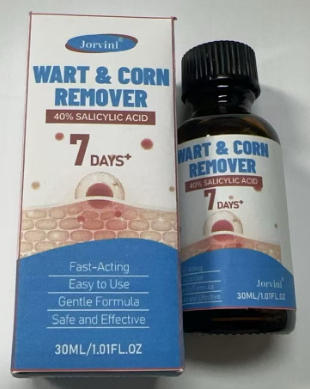 DRUG LABEL: Jorvinl WART AND CORN REMOVER
NDC: 87204-165 | Form: LIQUID
Manufacturer: Guangzhou Huixue Biotechnology Co., Ltd.
Category: otc | Type: HUMAN OTC DRUG LABEL
Date: 20260206

ACTIVE INGREDIENTS: SALICYLIC ACID 12 mg/30 mL
INACTIVE INGREDIENTS: WATER; HYALURONIC ACID; BISABOLOL; BORNEOL; ALLANTOIN; GLYCERIN

ACTIVE INGREDIENT

Salicylic Acid 40%

INACTIVE INGREDIENT

Water, Borneol, Glycerin, Polyethylene Glycol, Bisabolol, Allantoin, Lonicera Japonica (Honeysuckle) Flower Extract, Sophora Augustifolia Root Extract, Hyaluronic Acid, Aloe Vera Extract.

PURPOSE

Wart remover

INDICATIONS AND USAGE

For the removal of warts, including plantar warts, flat warts, common warts, corns, and calluses.

WARNINGS

For external use only. Flammable Keep away from fire and flame. Keep out of reach of children. Avoid contact with eyes, in case of contact, flush eyes with plenty of cool water Do not swallow, if swallowed, seek medical attention or contact a Poison Control Center (1-800-222-1222) immediately.

KEEP OUT OF REACH OF CHILDREN

Store at room temnerature Avnid excessive heat ahove 37°C (99°F) Skin discoloration may occur during or after use.

WHEN USING

1.Clean the affected area. You can soak the affected area in warm water for 5 minutes (optional). 2. Dip the liquid with the brush and apply iton the affected area. Ensure complete coverage, Let it dry. 3. Repeat this process 2-3 times daily until the skin looks smooth. 4. More severe may require more time.Patience and perseverance are required during its use. The longest continuous use period is no more than 12 weeks.

DO NOT USE

On irritated skin or on any area that is infct . If you are allergic to any ingredient in this product. . On moles, birthmarks, warts with hair growing from them, genital warts or warts on the face or mucous membranes. .If you have diabetes or poor blood circulation. .If you are pregnant or breastfeeding unless directed by a healthcare practitioner.

STOP USE

Chest pain, rapid heart beat, faintness, or dizziness occurs sudden, unexplained weight gain occurs,your hands or feet swell.

DOSAGE AND ADMINISTRATION

Twice each day,(1ml)each time.15 days supply